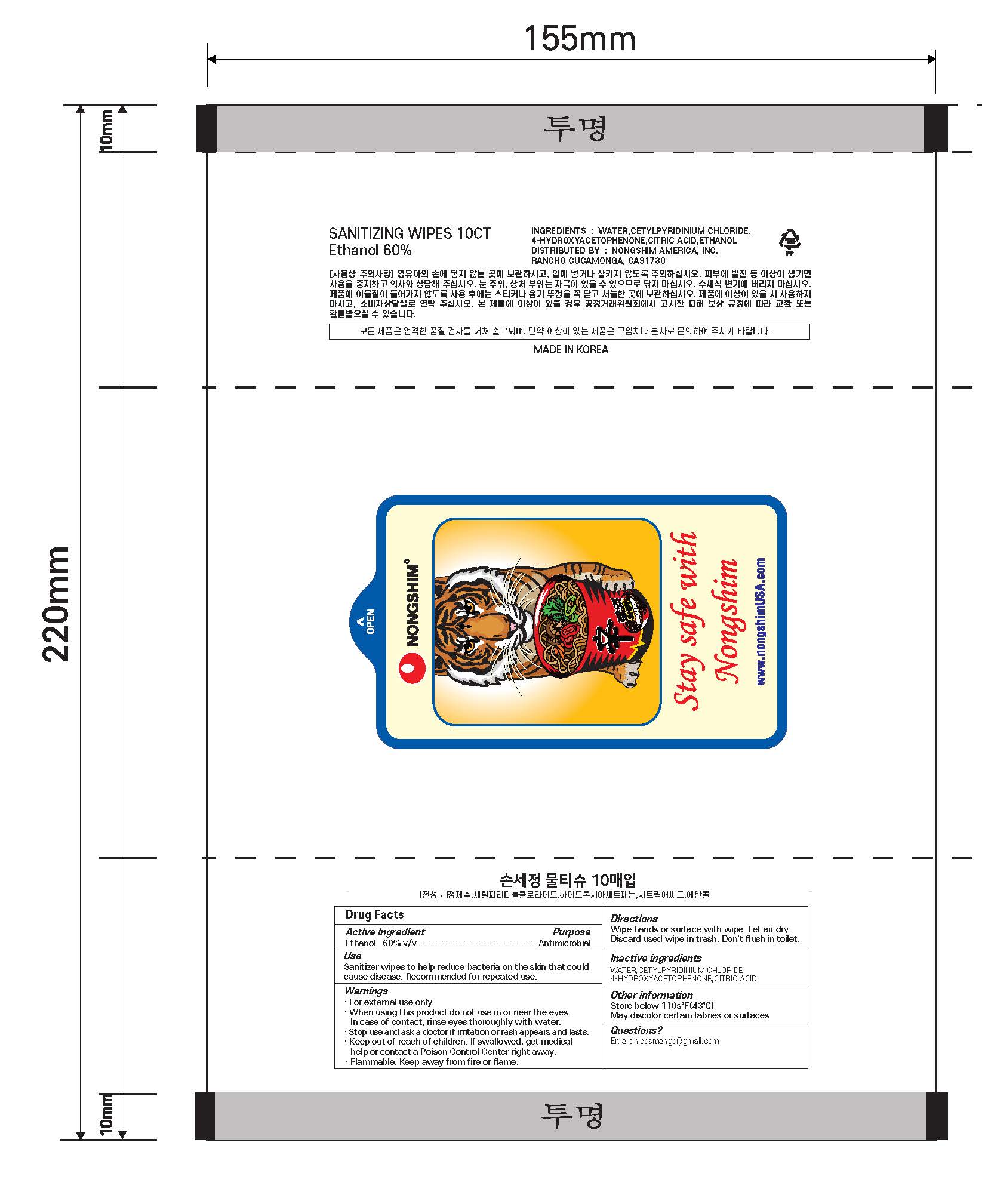 DRUG LABEL: Etiquette Sterilization wet wipes
NDC: 81582-0001 | Form: LIQUID
Manufacturer: YOOSEUNG IN NATURE Co.,Ltd
Category: otc | Type: HUMAN OTC DRUG LABEL
Date: 20230510

ACTIVE INGREDIENTS: ALCOHOL 60 g/100 1
INACTIVE INGREDIENTS: WATER; HYDROXYACETOPHENONE; CETYLPYRIDINIUM CHLORIDE; CITRIC ACID MONOHYDRATE

ACTIVE INGREDIENT

Alcohol (Ethanol)

INACTIVE INGREDIENT

WATER, CETYLPYRIDINIUM CHLORIDE, 4-HYDROXYACETOPHENONE, CITRIC ACID

PURPOSE

antiseptic

keep out of reach of the children

INDICATIONS AND USAGE

· Open, gently pull back resealable label, remove and use wipe as required.
· Reseal back after use to avoid evaporation of alcohol.

WARNINGS

For external use only.
DO NOT REPLACE WIPES USED FOR MEDICAL PROCEDURES. THESE WIPES ARE MEANT FOR GENERAL CLEANSING.

CAUTION:
1. Flammable. Use only in a well-ventilated area. Keep away from flames, such as a pilot light, and any object that sparks, such as an electric motor.
2. For external use only. Avoid contact with eyes or inner mouth. If contact occurs, rinse eyes thoroughly with running water. Do not use on compromised skin.
Discontinue use if rash or irritation occurs and consult a doctor. Wash hands thoroughly after handling.
3. Store in a cool dry place. Avoid heat or direct sunlight. Keep seal closed between use to retain moisture.
4. Do not flush. Dispose in a trash receptacle.
5. Keep out of reach of children unless under adult supervision.

DOSAGE AND ADMINISTRATION

for external use only